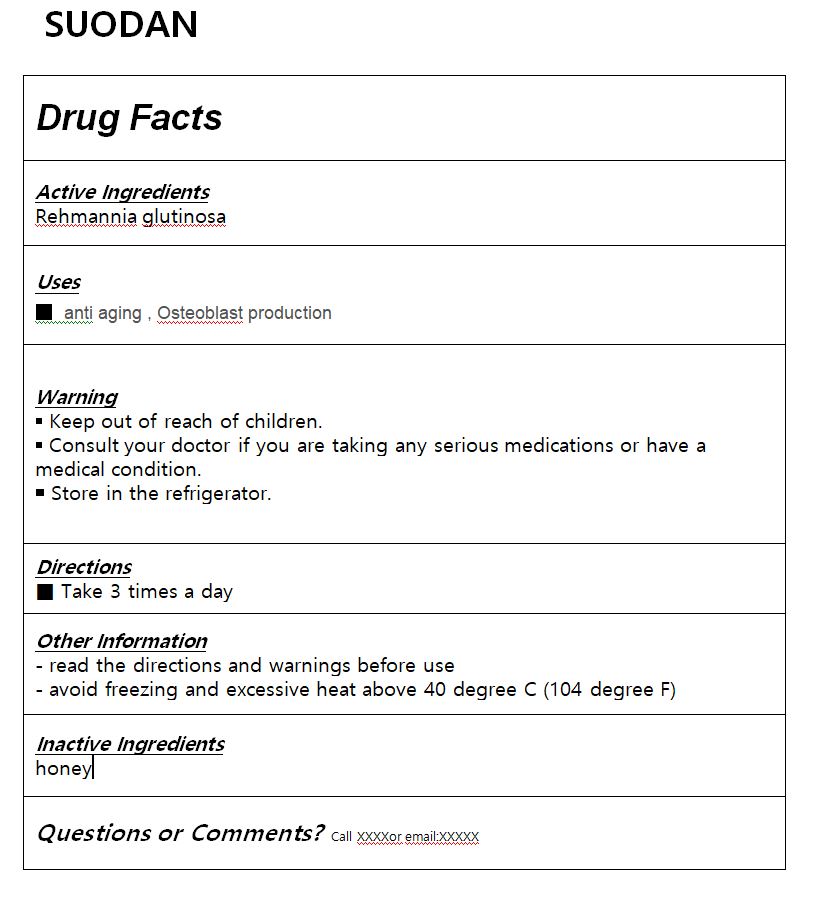 DRUG LABEL: SUODAN
NDC: 82230-0003 | Form: TABLET
Manufacturer: Dong woo dang pharmacy Co.,Ltd.
Category: otc | Type: HUMAN OTC DRUG LABEL
Date: 20210913

ACTIVE INGREDIENTS: REHMANNIA GLUTINOSA WHOLE 3 g/1 1
INACTIVE INGREDIENTS: VITAMIN D

Drug Facts

ACTIVE INGREDIENT

Rehmannia glutinosa

PURPOSE

anti aging
Osteoblast production

KEEP OUT OF REACH OF THE CHILDREN

INDICATIONS AND USAGE

Take 3 times a day

WARNINGS

■ For external use only.

■ Do not use in eyes.

■ lf swallowed, get medical help promptly.

■ Stop use, ask doctor lf irritation occurs.

■ Keep out of reach of children.

DOSAGE AND ADMINISTRATION

for external use only

INACTIVE INGREDIENT

Water